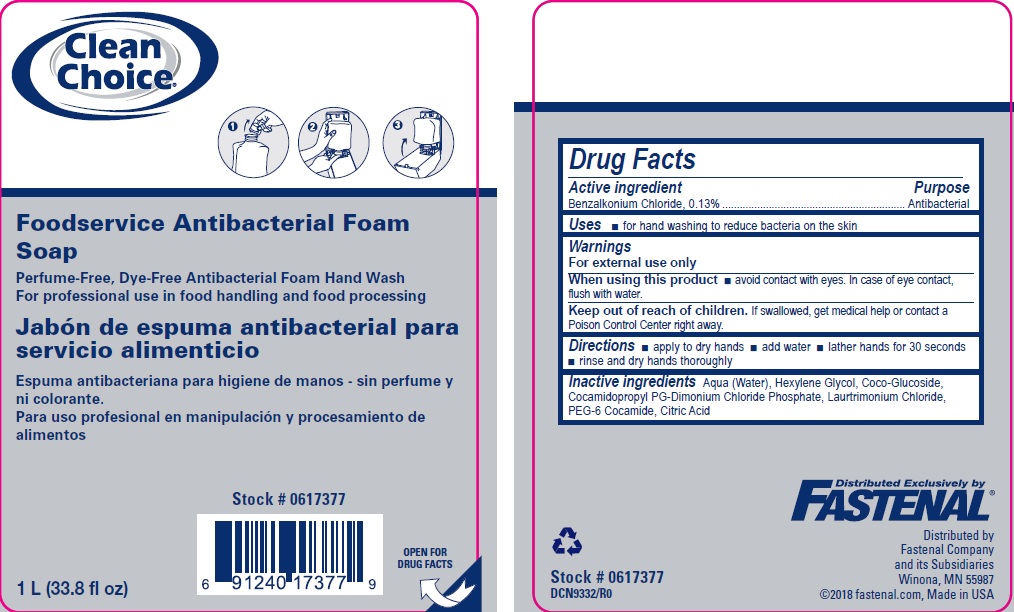 DRUG LABEL: Clean Choice Foodservice Antibacterial Foam
NDC: 11084-025 | Form: SOLUTION
Manufacturer: SC Johnson Professional USA, Inc.
Category: otc | Type: HUMAN OTC DRUG LABEL
Date: 20250131

ACTIVE INGREDIENTS: BENZALKONIUM CHLORIDE .13 g/100 mL
INACTIVE INGREDIENTS: WATER; HEXYLENE GLYCOL; COCO-GLUCOSIDE; COCAMIDOPROPYL PROPYLENE GLYCOL-DIMONIUM CHLORIDE PHOSPHATE; LAURTRIMONIUM CHLORIDE; PEG-6 COCAMIDE; ANHYDROUS CITRIC ACID

Drug Facts

Active ingredient

Benzalkonium Chloride, 0.13%

Purpose

Antibacterial

Uses

for hand washing to reduce bacteria on the skin

Warnings

For external use only

When using this product

avoid contact with eyes. In case of eye contact, flush with water.

Keep out of reach of children.

If swallowed, get medical help or contact a Poison Control Center right away.

Directions

apply to dry hands

add water

lather hands for 30 seconds

rinse and dry hands thoroughly

Inactive ingredients

Aqua (Water), Hexylene Glycol, Coco-Glucoside, Cocamidopropyl PG-Dimonium Chloride Phosphate, Laurtrimonium Chloride, PEG-6 Cocamide, Citric Acid

PACKAGE LABEL

Clean Choice

Foodservice Antibacterial Foam
Soap
Perfume-Free, Dye-Free Antibacterial Foam Hand Wash
For professional use in food handling and food processing
Jabón de espuma antibacterial para
servicio alimenticio
Espuma antibacteriana para higiene de manos - sin perfume y
ni colorante.
Para uso profesional en manipulación y procesamiento de
alimentos
Stock # 0617377
1 L (33.8 fl oz)
OPEN FOR
DRUG FACTS